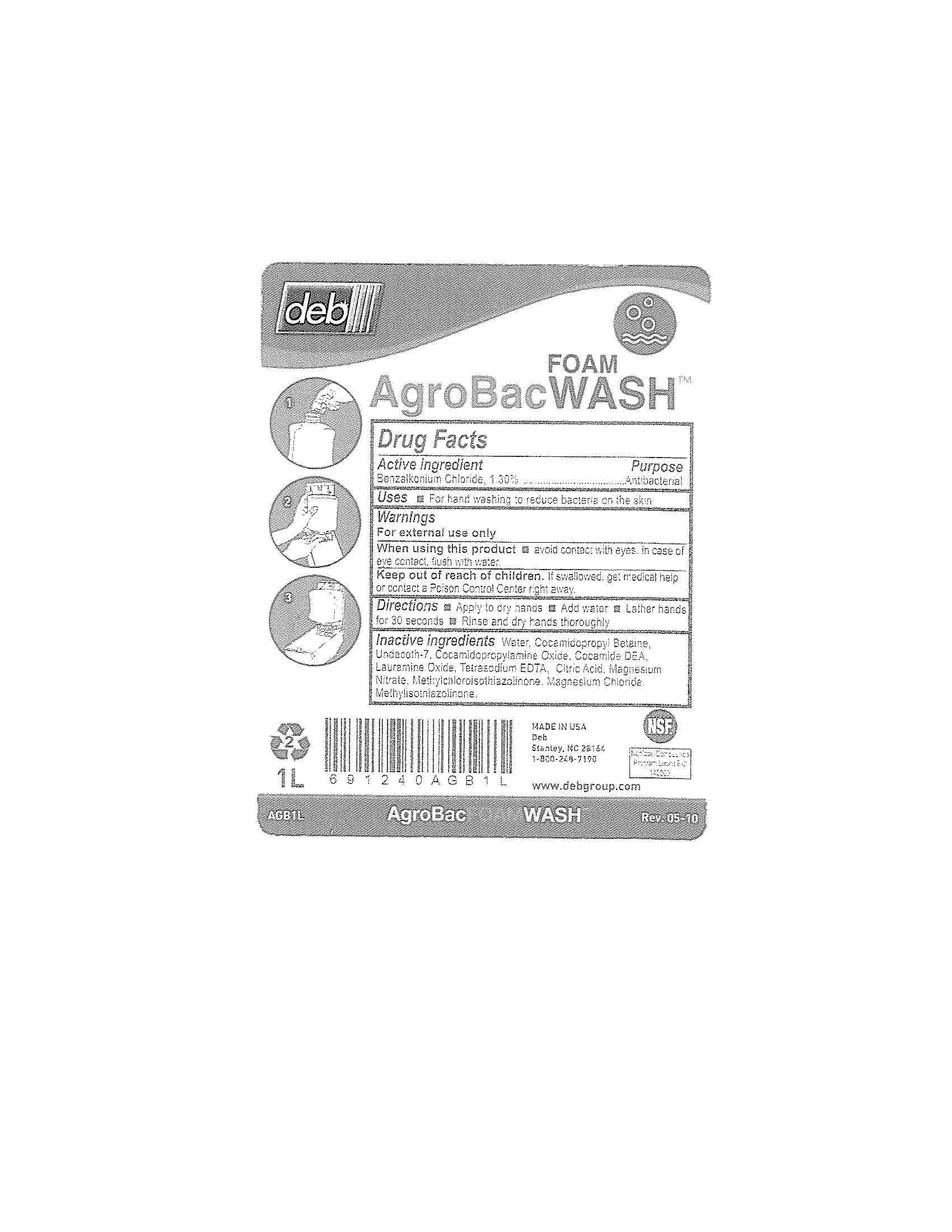 DRUG LABEL: AgroBac Foam Wash
NDC: 11084-054 | Form: LIQUID
Manufacturer: Deb USA, Inc.
Category: otc | Type: HUMAN OTC DRUG LABEL
Date: 20100910

ACTIVE INGREDIENTS: BENZALKONIUM CHLORIDE 1.30 mL/100 mL
INACTIVE INGREDIENTS: WATER; COCAMIDOPROPYL BETAINE; COCO DIETHANOLAMIDE; LAURAMINE OXIDE; EDETATE SODIUM; CITRIC ACID MONOHYDRATE; MAGNESIUM NITRATE; METHYLCHLOROISOTHIAZOLINONE; MAGNESIUM CHLORIDE; METHYLISOTHIAZOLINONE

Drug Facts

Active ingredient

Benzalkonium Chloride, 1.30%

Purpose

Antibacterial

Uses

For hand washing to reduce bacteria on the skin

Warnings

For external use only

When using this product avoid contact with eyes.

In case of eye contact, flush with water.

Keep out of reach of children.

If swallowed, get medical help or contact a Poison Control Center right away.

Directions

Apply to dry hands

Add water

Lather hands for 30 seconds

Rinse and dry hands thoroughly

Inactive ingredients

Water, Cocamidopropyl Betaine, Undeceth-7, Cocamidopropylamine Oxide, Cocamide DEA, Lauramine Oxide, Tetrasodium EDTA, Citric Acid, Magnesium Nitrate, Methylchloroisothiazolinone, Magnesium Chloride, Methylisothiazolinone.

PACKAGE LABEL

deb

AgroBac Foam Wash

MADE IN USE

NSF

Nonfood Compounds Program Listed E-2 140060

1L